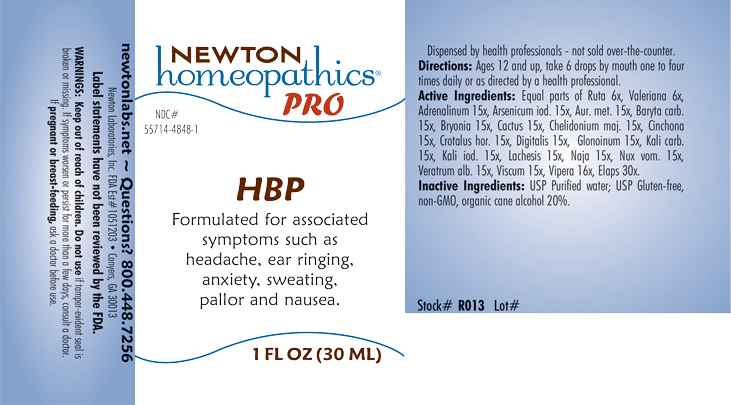 DRUG LABEL: HBP
NDC: 55714-4848 | Form: LIQUID
Manufacturer: Newton Laboratories, Inc.
Category: homeopathic | Type: HUMAN OTC DRUG LABEL
Date: 20230509

ACTIVE INGREDIENTS: MICRURUS CORALLINUS VENOM 30 [hp_X]/1 mL; VISCUM ALBUM FRUITING TOP 15 [hp_X]/1 mL; RUTA GRAVEOLENS FLOWERING TOP 6 [hp_X]/1 mL; VIPERA BERUS VENOM 16 [hp_X]/1 mL; EPINEPHRINE 15 [hp_X]/1 mL; ARSENIC TRIIODIDE 15 [hp_X]/1 mL; GOLD 15 [hp_X]/1 mL; BARIUM CARBONATE 15 [hp_X]/1 mL; BRYONIA ALBA ROOT 15 [hp_X]/1 mL; SELENICEREUS GRANDIFLORUS STEM 15 [hp_X]/1 mL; CHELIDONIUM MAJUS 15 [hp_X]/1 mL; CINCHONA OFFICINALIS BARK 15 [hp_X]/1 mL; CROTALUS HORRIDUS HORRIDUS VENOM 15 [hp_X]/1 mL; DIGITALIS 15 [hp_X]/1 mL; NITROGLYCERIN 15 [hp_X]/1 mL; POTASSIUM CARBONATE 15 [hp_X]/1 mL; POTASSIUM IODIDE 15 [hp_X]/1 mL; LACHESIS MUTA VENOM 15 [hp_X]/1 mL; NAJA NAJA VENOM 15 [hp_X]/1 mL; STRYCHNOS NUX-VOMICA SEED 15 [hp_X]/1 mL; VERATRUM ALBUM ROOT 15 [hp_X]/1 mL; VALERIAN 6 [hp_X]/1 mL
INACTIVE INGREDIENTS: WATER; ALCOHOL

HBP 4848L

INDICATIONS & USAGE SECTION

Formulated for associated symptoms such as headache, ear ringing, anxiety, sweating, pallor and nausea.

DOSAGE & ADMINISTRATION SECTION

Directions: Ages 12 and up, take 6 drops by mouth one to four times daily or as directed by a health professional.

OTC - ACTIVE INGREDIENT SECTION

Equal parts of Ruta graveolens 6x, Valeriana officinalis 6x, Adrenalinum 15x, Arsenicum iodatum 15x, Aurum metallicum 15x, Baryta carbonica 15x, Bryonia 15x, Cactus grandiflorus 15x, Chelidonium majus 15x, Cinchona officinalis 15x, Crotalus horridus 15x, Digitalis purpurea 15x, Glonoinum 15x, Kali carbonicum 15x, Kali iodatum 15x, Lachesis mutus 15x, Naja tripudians 15x, Nux vomica 15x, Veratrum album 15x, Vipera berus 16x, Viscum album 15x, Elaps corallinus 30x.

OTC - PURPOSE SECTION

Formulated for associated symptoms such as headache, ear ringing, anxiety, sweating, pallor and nausea.

INACTIVE INGREDIENT SECTION

Inactive Ingredients: USP Purified Water; USP Gluten-free, non-GMO, organic cane alcohol 20%.

QUESTIONS SECTION

newtonlabs.net - Questions? 800.448.7256

Newton Laboratories, Inc. FDA Est # 1051203 Conyers, GA 30013

WARNINGS SECTION

WARNINGS: Keep out of reach of children. Do not use if tamper-evident seal is broken or missing. If symptoms worsen or persist for more than a few days, consult a doctor. If pregnant or breast-feeding, ask a doctor before use.

OTC - PREGNANCY OR BREAST FEEDING SECTION

If pregnant or breast-feeding, ask a doctor before use.

OTC - KEEP OUT OF REACH OF CHILDREN SECTION

Keep out of reach of children.